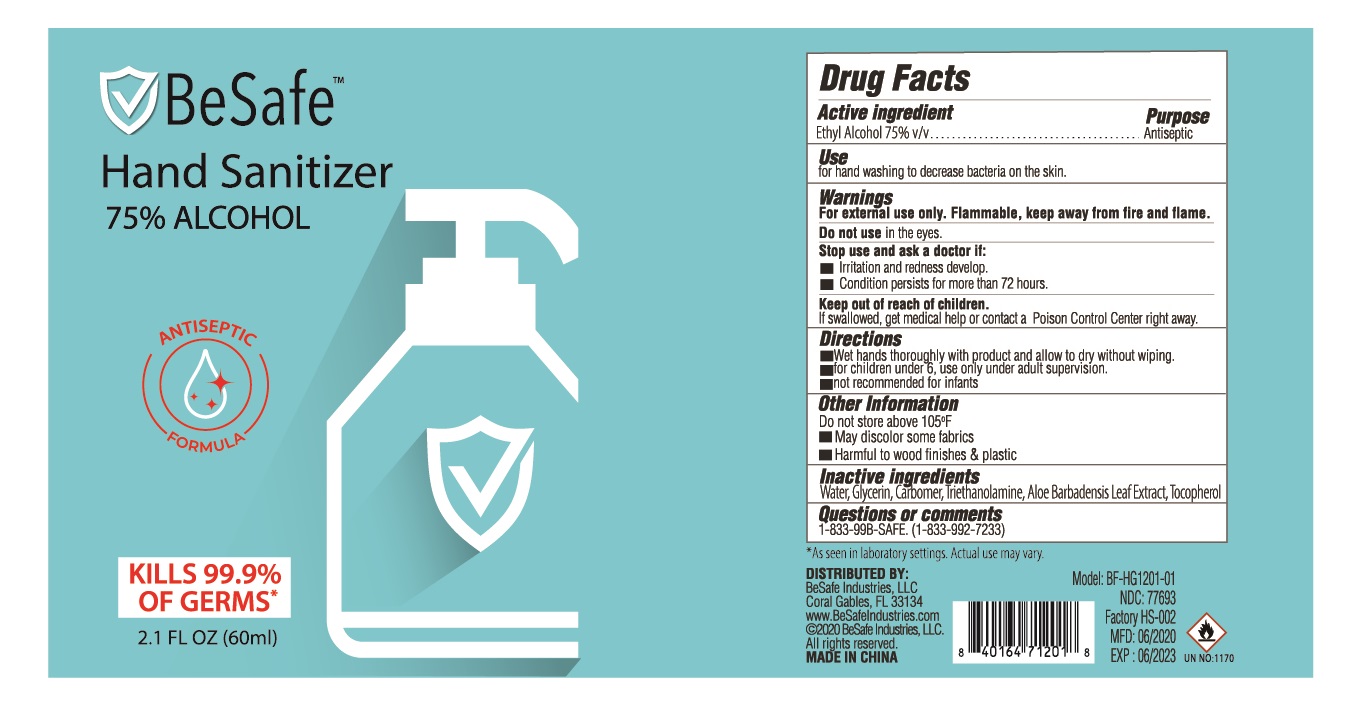 DRUG LABEL: Besafe
NDC: 75742-011 | Form: GEL
Manufacturer: Zhejiang Guoyao Jingyue Aerosol Co., Ltd.
Category: otc | Type: HUMAN OTC DRUG LABEL
Date: 20200710

ACTIVE INGREDIENTS: ALCOHOL 75 mL/100 mL
INACTIVE INGREDIENTS: TROLAMINE; WATER; GLYCERIN; CARBOMER 940; ALOE VERA LEAF; .ALPHA.-TOCOPHEROL, DL-

Besafe Hand Sanitizer

Active Ingredient

Ethyl Alcohol 75% v/v

Purpose

Antiseptic

Use

for hand washing to decrease bacteria on the skin.

Warnings

For external use only. Flammable, keep away from fire and flame.

Do not use in the eyes.

Stop use and ask a doctor if:

- Irritation and redness develop.
- condition persists for more than 72 hours.

Keep out of reach of children.

DO NOT USE

If swallowed, get medical help or contact a poison control center right away.

Directions

- Wet hands thoroughly with product and allow to dry without wiping.
- for children under 6, use only under adult supervision.
- not recommended for infants.

Other information

Do not store above 105oF

- May discolor some fabrics
- Harmful to wood finishes & plastic

Inactive Ingredients

Water, Glycerin, Carbomer, Triethanolamine, Aloe Barbadensis Leaf Extract, Tocopherol